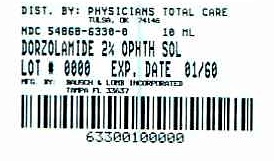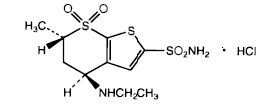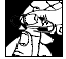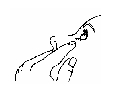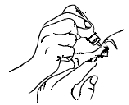 DRUG LABEL: Dorzolamide HCl
NDC: 54868-6330 | Form: SOLUTION/ DROPS
Manufacturer: Physicians Total Care, Inc.
Category: prescription | Type: HUMAN PRESCRIPTION DRUG LABEL
Date: 20120327

ACTIVE INGREDIENTS: DORZOLAMIDE HYDROCHLORIDE 22.3 mg/1 mL
INACTIVE INGREDIENTS: BENZALKONIUM CHLORIDE; HYDROXYETHYL CELLULOSE (2000 CPS AT 1%); MANNITOL; TRISODIUM CITRATE DIHYDRATE; SODIUM HYDROXIDE; WATER

Dorzolamide HCl Ophthalmic Solution, 2%

Sterile

DESCRIPTION

Dorzolamide HCl Ophthalmic Solution is a carbonic anhydrase inhibitor formulated for topical ophthalmic use.

Dorzolamide hydrochloride is described chemically as: (4S-trans)-4-(ethylamino)-5,6-dihydro-6-methyl-4H-thieno[2,3-b]thiopyran-2-sulfonamide 7,7-dioxide monohydrochloride. Dorzolamide hydrochloride is optically active. The specific rotation is

α 25° (C=1, water) = ~ -17°.

405

Its empirical formula is C10H16N2O4S3•HCl and its structural formula is

Dorzolamide hydrochloride has a molecular weight of 360.9 and a melting point of about 264°C. It is a white to off-white, crystalline powder, which is soluble in water and slightly soluble in methanol and ethanol.

Dorzolamide HCl Ophthalmic Solution is supplied as a sterile, isotonic, buffered, slightly viscous, aqueous solution of dorzolamide hydrochloride. The pH of the solution is approximately 5.6, and the osmolarity is 260-330 mOsM. Each mL of Dorzolamide HCl Ophthalmic Solution 2% contains 20 mg dorzolamide (22.3 mg of dorzolamide hydrochloride). Inactive ingredients are hydroxyethyl cellulose, mannitol, sodium citrate dihydrate, sodium hydroxide (to adjust pH) and water for injection. Benzalkonium chloride 0.0075% is added as a preservative.

CLINICAL PHARMACOLOGY

Mechanism of Action

Carbonic anhydrase (CA) is an enzyme found in many tissues of the body including the eye. It catalyzes the reversible reaction involving the hydration of carbon dioxide and the dehydration of carbonic acid. In humans, carbonic anhydrase exists as a number of isoenzymes, the most active being carbonic anhydrase II (CA-II), found primarily in red blood cells (RBCs), but also in other tissues. Inhibition of carbonic anhydrase in the ciliary processes of the eye decreases aqueous humor secretion, presumably by slowing the formation of bicarbonate ions with subsequent reduction in sodium and fluid transport. The result is a reduction in intraocular pressure (IOP).

Dorzolamide HCl Ophthalmic Solution contains dorzolamide hydrochloride, an inhibitor of human carbonic anhydrase II. Following topical ocular administration, Dorzolamide HCl Ophthalmic Solution reduces elevated intraocular pressure. Elevated intraocular pressure is a major risk factor in the pathogenesis of optic nerve damage and glaucomatous visual field loss.

Pharmacokinetics/Pharmacodynamics

When topically applied, dorzolamide reaches the systemic circulation. To assess the potential for systemic carbonic anhydrase inhibition following topical administration, drug and metabolite concentrations in RBCs and plasma and carbonic anhydrase inhibition in RBCs were measured.

Dorzolamide accumulates in RBCs during chronic dosing as a result of binding to CA-II. The parent drug forms a single N-desethyl metabolite, which inhibits CA-II less potently than the parent drug but also inhibits CA-I. The metabolite also accumulates in RBCs where it binds primarily to CA-I. Plasma concentrations of dorzolamide and metabolite are generally below the assay limit of quantitation (15nM).

Dorzolamide binds moderately to plasma proteins (approximately 33%). Dorzolamide is primarily excreted unchanged in the urine; the metabolite also is excreted in urine. After dosing is stopped, dorzolamide washes out of RBCs nonlinearly, resulting in a rapid decline of drug concentration initially, followed by a slower elimination phase with a half-life of about four months.

To simulate the systemic exposure after long-term topical ocular administration, dorzolamide was given orally to eight healthy subjects for up to 20 weeks. The oral dose of 2 mg b.i.d. closely approximates the amount of drug delivered by topical ocular administration of Dorzolamide HCl Ophthalmic Solution 2% t.i.d. Steady state was reached within 8 weeks. The inhibition of CA-II and total carbonic anhydrase activities was below the degree of inhibition anticipated to be necessary for a pharmacological effect on renal function and respiration in healthy individuals.

Clinical Studies

The efficacy of Dorzolamide HCl Ophthalmic Solution was demonstrated in clinical studies in the treatment of elevated intraocular pressure in patients with glaucoma or ocular hypertension (baseline IOP ≥ 23 mmHg). The IOP-lowering effect of Dorzolamide HCl Ophthalmic Solution was approximately 3 to 5 mmHg throughout the day and this was consistent in clinical studies of up to one year duration.

The efficacy of Dorzolamide HCl Ophthalmic Solution when dosed less frequently than three times a day (alone or in combination with other products) has not been established.

In a one year clinical study, the effect of Dorzolamide HCl Ophthalmic Solution 2% t.i.d. on the corneal endothelium was compared to that of betaxolol ophthalmic solution b.i.d. and timolol maleate ophthalmic solution 0.5% b.i.d. There were no statistically significant differences between groups in corneal endothelial cell counts or in corneal thickness measurements. There was a mean loss of approximately 4% in the endothelial cell counts for each group over the one year period.

INDICATIONS AND USAGE

Dorzolamide HCl Ophthalmic Solution is indicated in the treatment of elevated intraocular pressure in patients with ocular hypertension or open-angle glaucoma.

CONTRAINDICATIONS

Dorzolamide HCl Ophthalmic Solution is contraindicated in patients who are hypersensitive to any component of this product.

WARNINGS

Dorzolamide HCl Ophthalmic Solution is a sulfonamide and, although administered topically, is absorbed systemically. Therefore, the same types of adverse reactions that are attributable to sulfonamides may occur with topical administration with Dorzolamide HCl Ophthalmic Solution. Fatalities have occurred, although rarely, due to severe reactions to sulfonamides including Stevens-Johnson syndrome, toxic epidermal necrolysis, fulminant hepatic necrosis, agranulocytosis, aplastic anemia, and other blood dyscrasias. Sensitization may recur when a sulfonamide is readministered irrespective of the route of administration. If signs of serious reactions or hypersensitivity occur, discontinue the use of this preparation.

PRECAUTIONS

General

The management of patients with acute angle-closure glaucoma requires therapeutic interventions in addition to ocular hypotensive agents. Dorzolamide HCl Ophthalmic Solution has not been studied in patients with acute angle-closure glaucoma.

Dorzolamide HCl Ophthalmic Solution has not been studied in patients with severe renal impairment (CrCl < 30 mL/min). Because Dorzolamide HCl Ophthalmic Solution and its metabolite are excreted predominantly by the kidney, Dorzolamide HCl Ophthalmic Solution is not recommended in such patients.

Dorzolamide HCl Ophthalmic Solution has not been studied in patients with hepatic impairment and should therefore be used with caution in such patients.

In clinical studies, local ocular adverse effects, primarily conjunctivitis and lid reactions, were reported with chronic administration of Dorzolamide HCl Ophthalmic Solution. Many of these reactions had the clinical appearance and course of an allergic-type reaction that resolved upon discontinuation of drug therapy. If such reactions are observed, Dorzolamide HCl Ophthalmic Solution should be discontinued and the patient evaluated before considering restarting the drug. (See ADVERSE REACTIONS)

There is a potential for an additive effect on the known systemic effects of carbonic anhydrase inhibition in patients receiving an oral carbonic anhydrase inhibitor and Dorzolamide HCl Ophthalmic Solution. The concomitant administration of Dorzolamide HCl Ophthalmic Solution and oral carbonic anhydrase inhibitors is not recommended.

There have been reports of bacterial keratitis associated with the use of multiple-dose containers of topical ophthalmic products. These containers had been inadvertently contaminated by patients who, in most cases, had a concurrent corneal disease or a disruption of the ocular epithelial surface. Choroidal detachment has been reported with administration of aqueous suppressant therapy (e.g., dorzolamide) after filtration procedures.

There is an increased potential for developing corneal edema in patients with low endothelial cell counts. Precautions should be used when prescribing Dorzolamide HCl Ophthalmic Solution to this group of patients.

Information for patients

Dorzolamide HCl Ophthalmic Solution is a sulfonamide and although administered topically is absorbed systemically. Therefore the same types of adverse reactions that are attributable to sulfonamides may occur with topical administration. Patients should be advised that if serious or unusual reactions or signs of hypersensitivity occur, they should discontinue the use of the product (see WARNINGS).

Patients should be advised that if they develop any ocular reactions, particularly conjunctivitis and lid reactions, they should discontinue use and seek their physician's advice.

Patients should be instructed to avoid allowing the tip of the dispensing container to contact the eye or surrounding structures.

Patients should also be instructed that ocular solutions, if handled improperly or if the tip of the dispensing container contacts the eye or surrounding structures, can become contaminated by common bacteria known to cause ocular infections. Serious damage to the eye and subsequent loss of vision may result from using contaminated solutions.

Patients also should be advised that if they have ocular surgery or develop an intercurrent ocular condition (e.g., trauma or infection), they should immediately seek their physician's advice concerning the continued use of the present multidose container.

If more than one topical ophthalmic drug is being used, the drugs should be administered at least ten minutes apart.

Patients should be advised that Dorzolamide HCl Ophthalmic Solution contains benzalkonium chloride which may be absorbed by soft contact lenses. Contact lenses should be removed prior to administration of the solution. Lenses may be reinserted 15 minutes following Dorzolamide HCl Ophthalmic Solution administration.

Drug interactions

Although acid-base and electrolyte disturbances were not reported in the clinical trials with Dorzolamide HCl Ophthalmic Solution, these disturbances have been reported with oral carbonic anhydrase inhibitors and have, in some instances, resulted in drug interactions (e.g., toxicity associated with high-dose salicylate therapy). Therefore, the potential for such drug interactions should be considered in patients receiving Dorzolamide HCl Ophthalmic Solution.

Carcinogenesis, mutagenesis, impairment of fertility

In a two-year study of dorzolamide hydrochloride administered orally to male and female Sprague-Dawley rats, urinary bladder papillomas were seen in male rats in the highest dosage group of 20 mg/kg/day (250 times the recommended human ophthalmic dose). Papillomas were not seen in rats given oral doses equivalent to approximately 12 times the recommended human ophthalmic dose. No treatment-related tumors were seen in a 21-month study in female and male mice given oral doses up to 75 mg/kg/day (~900 times the recommended human ophthalmic dose).

The increased incidence of urinary bladder papillomas seen in the high-dose male rats is a class effect of carbonic anhydrase inhibitors in rats. Rats are particularly prone to developing papillomas in response to foreign bodies, compounds causing crystalluria, and diverse sodium salts.

No changes in bladder urothelium were seen in dogs given oral dorzolamide hydrochloride for one year at 2 mg/kg/day (25 times the recommended human ophthalmic dose) or monkeys dosed topically to the eye at 0.4 mg/kg/day (~5 times the recommended human ophthalmic dose) for one year.

The following tests for mutagenic potential were negative: (1) in vivo (mouse) cytogenetic assay; (2) in vitro chromosomal aberration assay; (3) alkaline elution assay; (4) V-79 assay; and (5) Ames test.

In reproduction studies of dorzolamide hydrochloride in rats, there were no adverse effects on the reproductive capacity of males or females at doses up to 188 or 94 times, respectively, the recommended human ophthalmic dose.

Pregnancy

Teratogenic effects

Pregnancy Category C. Developmental toxicity studies with dorzolamide hydrochloride in rabbits at oral doses of ≥ 2.5 mg/kg/day (31 times the recommended human ophthalmic dose) revealed malformations of the vertebral bodies. These malformations occurred at doses that caused metabolic acidosis with decreased body weight gain in dams and decreased fetal weights. No treatment-related malformations were seen at 1.0 mg/kg/day (13 times the recommended human ophthalmic dose). There are no adequate and well-controlled studies in pregnant women. Dorzolamide HCl Ophthalmic Solution should be used during pregnancy only if the potential benefit justifies the potential risk to the fetus.

Nursing mothers

In a study of dorzolamide hydrochloride in lactating rats, decreases in body weight gain of 5 to 7% in offspring at an oral dose of 7.5 mg/kg/day (94 times the recommended human ophthalmic dose) were seen during lactation. A slight delay in postnatal development (incisor eruption, vaginal canalization and eye openings), secondary to lower fetal body weight, was noted.

It is not known whether this drug is excreted in human milk. Because many drugs are excreted in human milk and because of the potential for serious adverse reactions in nursing infants from Dorzolamide HCl Ophthalmic Solution, a decision should be made whether to discontinue nursing or to discontinue the drug, taking into account the importance of the drug to the mother.

Pediatric use

Safety and IOP-lowering effects of Dorzolamide HCl Ophthalmic Solution have been demonstrated in pediatric patients in a 3-month, multicenter, double-masked, active-treatment-controlled trial.

Geriatric use

No overall differences in safety or effectiveness have been observed between elderly and younger patients.

ADVERSE REACTIONS

Controlled clinical trials: The most frequent adverse events associated with Dorzolamide Hydrochloride Ophthalmic Solution were ocular burning, stinging, or discomfort immediately following ocular administration (approximately one-third of patients). Approximately one-quarter of patients noted a bitter taste following administration. Superficial punctate keratitis occurred in 10-15% of patients and signs and symptoms of ocular allergic reaction in approximately 10%. Events occurring in approximately 1-5% of patients were conjunctivitis and lid reactions (see PRECAUTIONS, General), blurred vision, eye redness, tearing, dryness, and photophobia.

Other ocular events and systemic events were reported infrequently, including headache, nausea, asthenia/fatigue; and, rarely, skin rashes, urolithiasis, and iridocyclitis.

In a 3-month, double-masked, active-treatment-controlled, multicenter study in pediatric patients, the adverse experience profile of Dorzolamide HCl Ophthalmic Solution was comparable to that seen in adult patients.

Clinical practice: The following adverse events have occurred either at low incidence (<1%) during clinical trials or have been reported during the use of Dorzolamide HCl Ophthalmic Solution in clinical practice where these events were reported voluntarily from a population of unknown size and frequency of occurrence cannot be determined precisely. They have been chosen for inclusion based on factors such as seriousness, frequency of reporting, possible causal connection to Dorzolamide HCl Ophthalmic Solution, or a combination of these factors: signs and symptoms of systemic allergic reactions including angioedema, bronchospasm, pruritus, and urticaria; dizziness, paresthesia; ocular pain, transient myopia, choroidal detachment following filtration surgery, eyelid crusting; dyspnea; contact dermatitis, epistaxis, dry mouth and throat irritation.

OVERDOSAGE

Electrolyte imbalance, development of an acidotic state, and possible central nervous system effects may occur. Serum electrolyte levels (particularly potassium) and blood pH levels should be monitored.

DOSAGE AND ADMINISTRATION

The dose is one drop of Dorzolamide HCl Ophthalmic Solution in the affected eye(s) three times daily.

Dorzolamide HCl Ophthalmic Solution may be used concomitantly with other topical ophthalmic drug products to lower intraocular pressure. If more than one topical ophthalmic drug is being used, the drugs should be administered at least ten minutes apart.

HOW SUPPLIED

Dorzolamide HCl Ophthalmic Solution is a slightly opalescent, nearly colorless, slightly viscous solution.

Dorzolamide HCl Ophthalmic Solution is supplied in a white low-density polyethylene (LDPE) bottle with a controlled drop tip and orange polypropylene cap in the following sizes:

10 mL in a 10 mL bottle NDC 54868-6330-0

STORAGE

Store Dorzolamide HCl Ophthalmic Solution at 20°-25°C (68°-77°F) [See USP Controlled Room Temperature]. Protect from light.

Rx only

Manufacturer Information

Bausch & Lomb Incorporated
Tampa, FL 33637
©Bausch & Lomb Incorporated

Revised December 2008

9080602 (Folded)

Additional barcode labeling by:

Physicians Total Care, Inc.

Tulsa, Oklahoma 74146

INSTRUCTIONS FOR USE

Dorzolamide HCl Ophthalmic Solution 2%

INSTRUCTIONS FOR USE

Please follow these instructions carefully when using Dorzolamide HCl Ophthalmic Solution 2%. Use Dorzolamide HCl Ophthalmic Solution 2% as prescribed by your doctor.

1. If you use other topically applied ophthalmic medications, they should be administered at least 10 minutes before or after Dorzolamide HCl Ophthalmic Solution 2%.

2. Wash hands before each use.

3. To open the bottle, remove the shrink neck band and unscrew the cap by turning counter clockwise.

4. Tilt your head back and pull your lower eyelid down slightly to form a pocket between your eyelid and your eye.

5. Instill drops as directed by your doctor.

OPHTHALMIC MEDICATIONS, IF HANDLED IMPROPERLY, CAN BECOME CONTAMINATED BY COMMON BACTERIA KNOWN TO CAUSE EYE INFECTIONS. SERIOUS DAMAGE TO THE EYE AND SUBSEQUENT LOSS OF VISION MAY RESULT FROM USING CONTAMINATED OPHTHALMIC MEDICATIONS. IF YOU THINK YOUR MEDICATION MAY BE CONTAMINATED, OR IF YOU DEVELOP AN EYE INFECTION, CONTACT YOUR DOCTOR IMMEDIATELY CONCERNING CONTINUED USE OF THIS BOTTLE.

6. Repeat steps 4 & 5 with the other eye if instructed to do so by your doctor.

WARNING: Keep out of reach of children.

If you have any questions about the use of Dorzolamide HCl Ophthalmic Solution 2%, please consult your doctor.

Revised December 2008

Bausch & Lomb Incorporated
Tampa, Florida 33637
© Bausch & Lomb Incorporated

9080602 (Folded)

PACKAGE/LABEL PRINCIPAL DISPLAY PANEL

NDC 54868-6330-0

Dorzolamide HCl Ophthalmic Solution, 2%*

Dorzolamide Equivalent (Dorzolamide hydrochloride 22.3 mg/mL)

Sterile

Rx only

FOR TOPICAL APPLICATION IN THE EYE